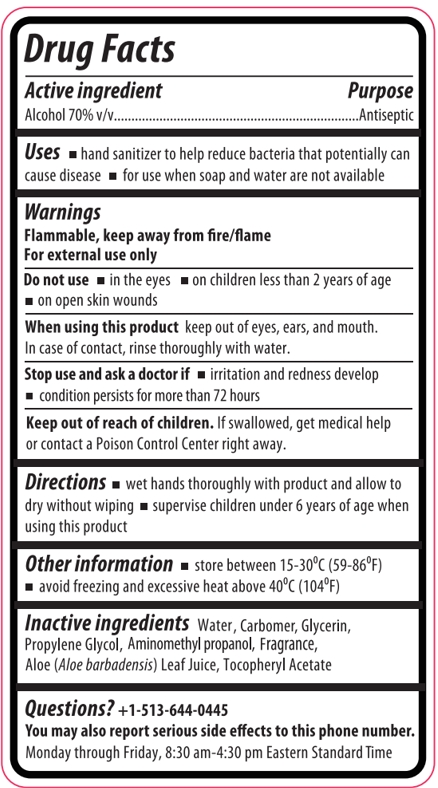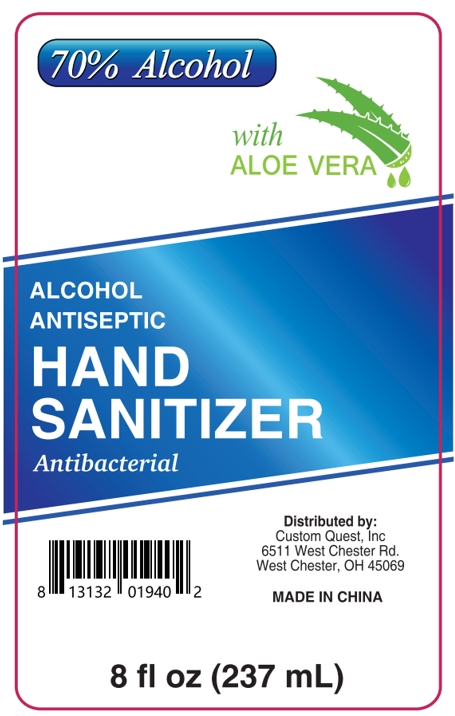 DRUG LABEL: ALCOHOL ANTISEPTIC HAND SANITIZER ANTIBACTERIAL
NDC: 75742-028 | Form: GEL
Manufacturer: Zhejiang Guoyao Jingyue Aerosol Co., Ltd.
Category: otc | Type: HUMAN OTC DRUG LABEL
Date: 20231214

ACTIVE INGREDIENTS: ALCOHOL 70 mL/100 mL
INACTIVE INGREDIENTS: GLYCERIN; ALOE VERA LEAF; .ALPHA.-TOCOPHEROL ACETATE; WATER; CARBOMER HOMOPOLYMER, UNSPECIFIED TYPE; PROPYLENE GLYCOL; AMINOMETHYLPROPANOL

Active ingredient

Alcohol 70% v/v

Purpose

Antiseptic

Uses

- Hand sanitizer to help reduce bacteria that potentially can cause disease
- for use when soap and water are not available

Warnings

Flammable, keep away from fire/ flame

For external use only

Do not use

- in the eyes
- on children less than 2 years of age
- on open skin wounds

When using

When using this product keep out of eyes, ears, and mouth, In case of contact, rinse thoroughly with water.

Stop use and ask a doctor if

- irritation and redness develop
- condition persists for more than 72 hours

Keep out of reach of children

if swallowed, get medical help or contact a Poison Control Center right away.

Directions

- wet hands thoroughly with product and allow to dry without wiping
- supervise children under 6 years of age when using this product.

Other information

- store between 15-30ºC (59-86ºF)
- avoid freezing and excessive heat above 40ºC(104ºF)

inactive ingredients

WATER, CARBOMER, GLYCERIN, PROPYLENE GLYCOL, AMINOMETHYL PROPANOL, FRAGRANCE, ALOE(ALOE BARBADENSIS)LEAF JUICE, TOCOPHERYL ACETATE